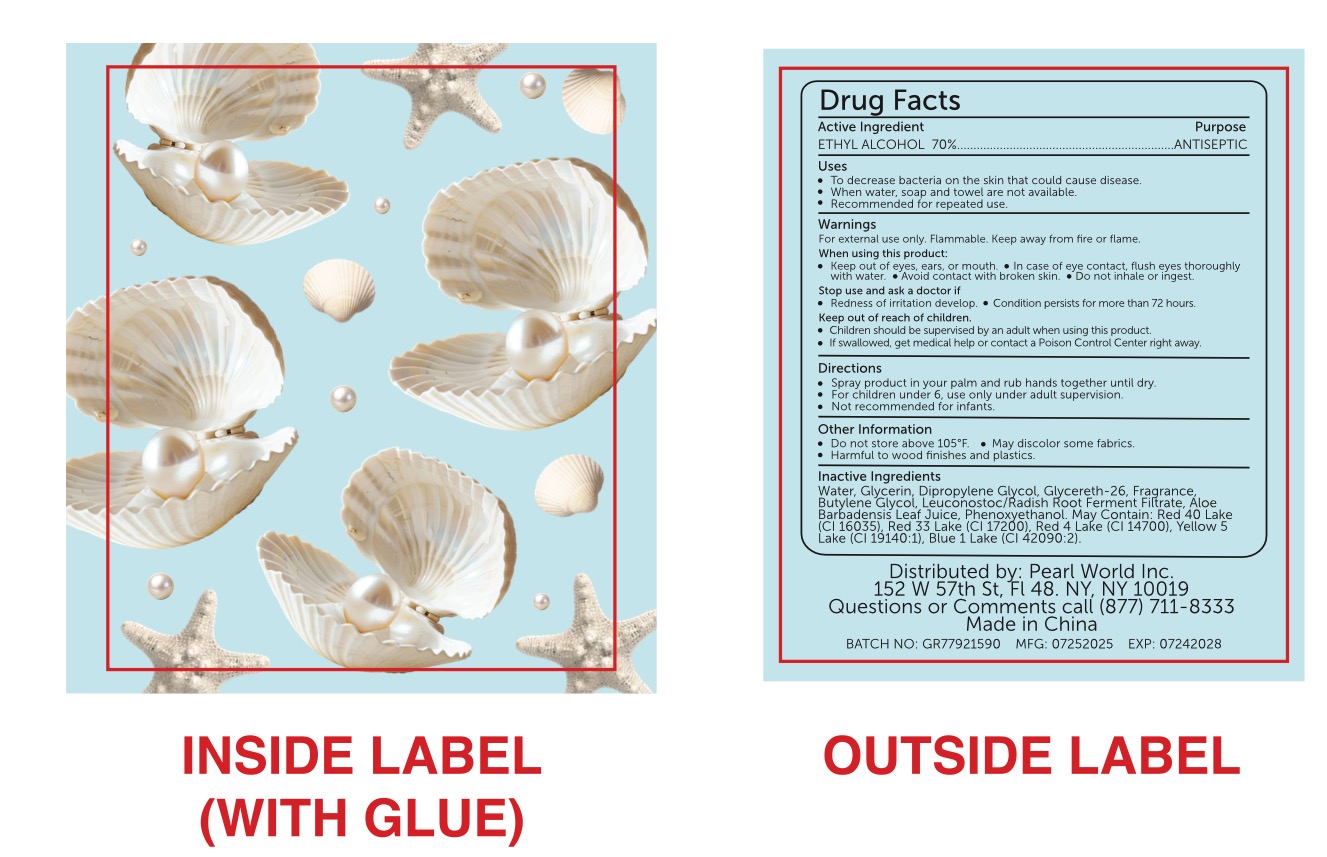 DRUG LABEL: Hand Sanitizer Mist
NDC: 85472-004 | Form: SPRAY
Manufacturer: Zhejiang Gaorong Cosmetic Co., Ltd.
Category: otc | Type: HUMAN OTC DRUG LABEL
Date: 20250725

ACTIVE INGREDIENTS: ALCOHOL 71 mL/100 mL
INACTIVE INGREDIENTS: LEUCONOSTOC/RADISH ROOT FERMENT FILTRATE; PHENOXYETHANOL; FD&C YELLOW NO. 5; FD&C BLUE NO. 1; BUTYLENE GLYCOL; ALOE BARBADENSIS LEAF JUICE; WATER; GLYCERETH-26; DIPROPYLENE GLYCOL; GLYCERIN

ACTIVE INGREDIENT

ETHYL ALCOHOL 70%

Purpose

ANTISEPTIC

Use

To decrease bacteria on the skin that could cause disease.

When water, soap and towel are not available.

Recommended for repeated use.

Warnings

For external use only. Flammable. Keep away from fire or flame.

Stop use and ask a doctor if

Redness of irritation develop.

Condition persists for more than 72 hours.

When using this product:

Keep out of eyes, ears, or mouth.

In case of eye contact, flush eyes thoroughly with water.

Avoid contact with broken skin.

Do not inhale or ingest.

Stop use and ask a doctor if

Redness of irritation develop.

Condition persists for more than 72 hours.

Directions

Spray product in your palm and rub hands together until dry.

For children under 6, use only under adult supervision.

Not recommended for infants.

Others information

Do not store above 105°F.

May discolor some fabrics.

Harmful to wood finishes and plastics.

Inactive ingredients

Water, Glycerin, Dipropylene Glycol, Glycereth-26, Fragrance, Butylene Glycol, Leuconostoc/Radish Root Ferment Filtrate, Aloe Barbadensis Leaf Juice, Phenoxyethanol. May Contain: Red 40 Lake (Cl 16035), Red 33 Lake (CI 17200), Red 4 Lake (CI 14700), Yellow 5 Lake (CI 19140:1), Blue 1 Lake (CI 42090:2)

KEEP OUT OF REACH OF CHILDREN

Children should be supervised by an adult when using this product.

If swallowed, get medical help or contact a Poison Control Center right away.